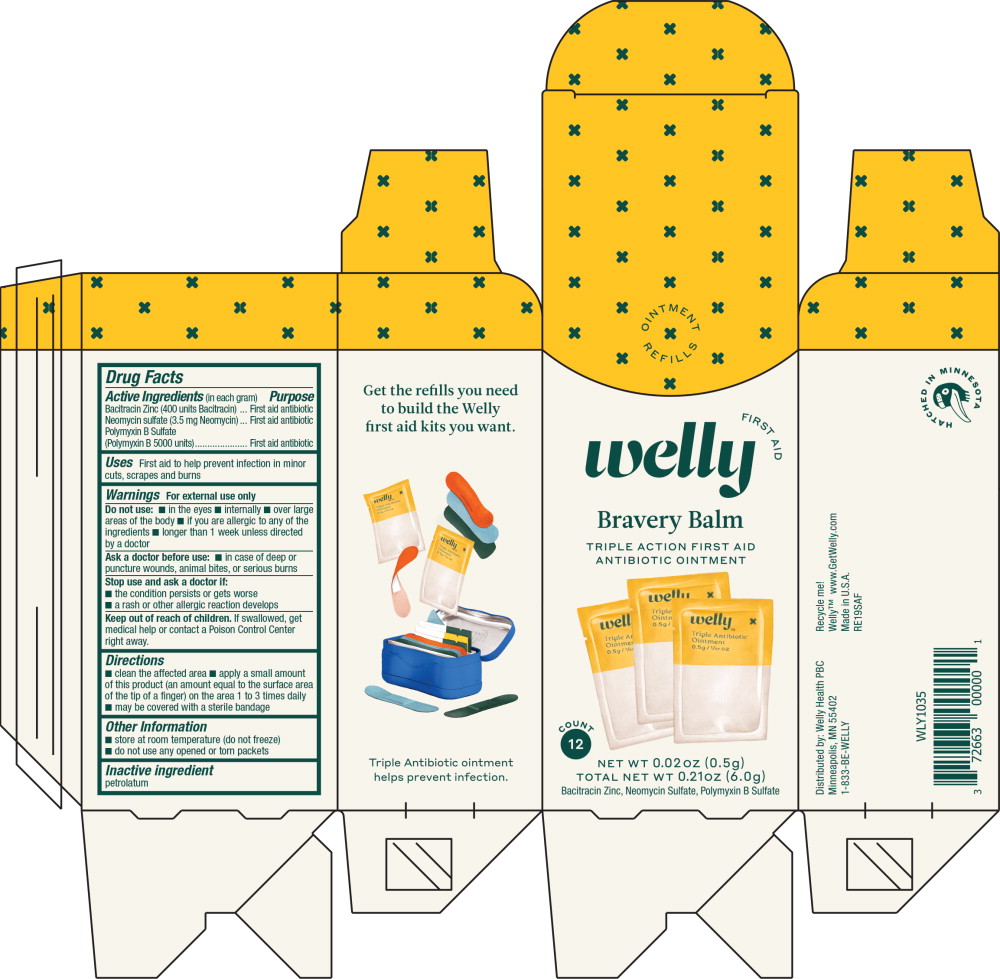 DRUG LABEL: Antibiotic
NDC: 72663-560 | Form: OINTMENT
Manufacturer: Welly Health PBC
Category: otc | Type: HUMAN OTC DRUG LABEL
Date: 20191105

ACTIVE INGREDIENTS: bacitracin zinc 400 [iU]/1 g; neomycin sulfate 3.5 mg/1 g; polymyxin b sulfate 5000 [iU]/1 g
INACTIVE INGREDIENTS: petrolatum

Drug Facts

Active ingredients (per gram)

Bacitracin Zinc 400 units

Neomycin Sulfate 3.5 mg

Polymyxin B Sulfate 5000 units

Purpose

First aid antibiotic

First aid antibiotic

First aid antibiotic

Uses

First aid to help prevent infection in minor cuts, scrapes and burns

Warnings

For external use only

Do not use:

- in the eyes
- internally
- over large of the body
- if you are allergic to any of the ingredients
- longer than 1 week unless directed by a doctor

Ask a doctor before use:

- in case of deep or puncture wounds, animal bites, or serious burns

Stop use and ask a doctor if:

- condition persists or gets worse
- a rash or other allergic reaction develops

Keep this and all drugs out of the reach of children.

In case of accidental ingestion, seek professional assistance or contact a Poison Control Center immediately

Directions

- Clean affected area
- Apply a small amount of this product (an amount equal to the surface area of tip of finger) on area 1 to 3 times daily
- May be covered with a sterile bandage

Other information

- Store at room temperature (do not freeze)
- Do not use any opened or torn packages

Inactive ingredient

white petrolatum

Principal Display Panel - 0.5g Carton Label

FIRST AID

welly

Bravely Balm

TRIPLE ACTION FIRST AID

ANTIBIOTIC OINTMENT

COUNT 12

NET WT 0.02 oz (0.5g)

TOTAL NET WT 0.21oz (6.0g)

Bacitracin Zinc, Neomycin Sulfate, Polymyxin B Sulfate